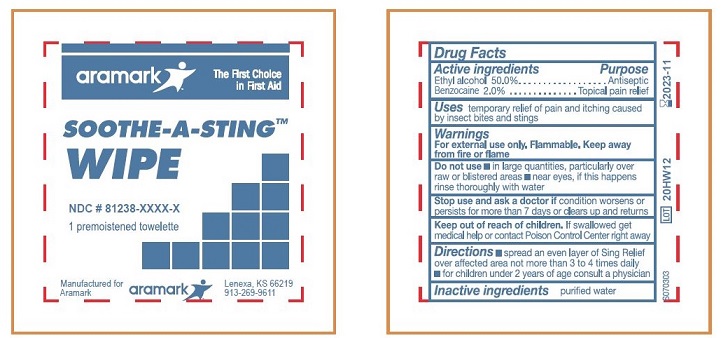 DRUG LABEL: Soothe-A-Sting
NDC: 81238-0315 | Form: CLOTH
Manufacturer: Western First Aid Safety dba Aramark
Category: otc | Type: HUMAN OTC DRUG LABEL
Date: 20210521

ACTIVE INGREDIENTS: ALCOHOL 0.50 mL/1 mL; BENZOCAINE 0.02 g/1 mL
INACTIVE INGREDIENTS: WATER

aramark Soothe-A-Sting

Drug Facts
Active Ingredients

Ethyl alcohol 50.0%

Benzocaine 2.0%

Purpose

Ethyl alcohol .......... Antiseptic

Benzocaine ........... Topical pain relief

INDICATIONS AND USAGE

Uses temporary relief of pain and itching caused by insect bites and stings.

Warnings

For external use only. Flammable. Keep away from fire or flame.

Do not use ■ in large quantities, particularly over

raw or blistered areas ■ near eyes, if this happens

winse thoroughly with water.

Stop use and ask a doctor if condition worsens or

persists for more than 7 days or clears up and returns

Keep out of reach of children. If swallowed, get
medical help or contact a Poison Control Center
right away.

DOSAGE AND ADMINISTRATION

Directions ■spread an even layer of Sing Relief

over affected area not mor than 3 to 4 times daily
■ for children under 2 years of age consult a physician

Inactive ingredients purified water

Product Label

aramark : The First Choice In First Aid

SOOTHE-A-STING™

WIPE

NDC # 81238-0315-1

1 premoistened towelette

Manufactured for Aramark

aramark Lenexa, KS 66219

913-269-9611

LOT

res